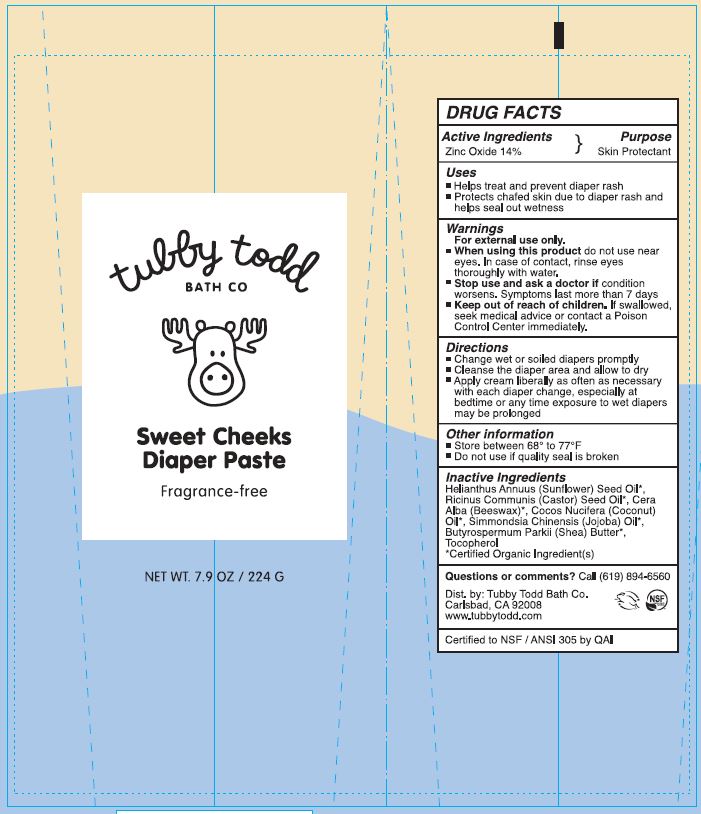 DRUG LABEL: Sweet Cheeks Diaper
NDC: 73088-301 | Form: PASTE
Manufacturer: Tubby Todd
Category: otc | Type: HUMAN OTC DRUG LABEL
Date: 20241217

ACTIVE INGREDIENTS: ZINC OXIDE 100 g/14 mL
INACTIVE INGREDIENTS: RICINUS COMMUNIS (CASTOR) SEED OIL; BEESWAX; SIMMONDSIA CHINENSIS (JOJOBA) SEED OIL; TOCOPHEROL; HELIANTHUS ANNUUS (SUNFLOWER) SEED OIL; CAPRYLIC/CAPRIC TRIGLYCERIDE; BUTYROSPERMUM PARKII (SHEA) BUTTER

Tubby Todd (as PLD) - Sweet Cheeks Diaper Paste (73088-301)

Active Ingredients

Zinc Oxide 14%

Purpose

Skin Protectant

Uses

- Helps treat and prevent diaper rash
- Protects chaftes skin due to diaper rash and helps seal out wetness

Warnings

For External Use Only

- When using this product do not use near eyes. In case of contact, rinse eyes thoroughly with water.
- Stop use and ask a doctor if condition worsens. Symptoms may last more than 7 days

Keep out of reach of children.

If swallowed, seek medical advice or contact a Poison Control Center immediately.

Directions

Change wet or soiled diapers promptly
Cleanse the diaper area and allow to dry
Apply cream liberally as often as necessary with each diaper change, especially at bedtime or any time exposure to wet diapers may be prolonged

Other information

Store between 68° to 77°F
Do not use if quality seal is broken

Inactive ingredients

Beeswax*, Butyrospermum Parkii (Shea) Butter*, Caprylic/Capric Triglyceride*, Helianthus Annuus (Sunflower) Seed Oil*, Ricinus Communis (Castor) Seed Oil*, Simmondsia Chinensis (Jojoba) Oil*, Tocopherol

*Certified Organic Ingredient(s)

Questions or comments?

Call (619) 894-6540